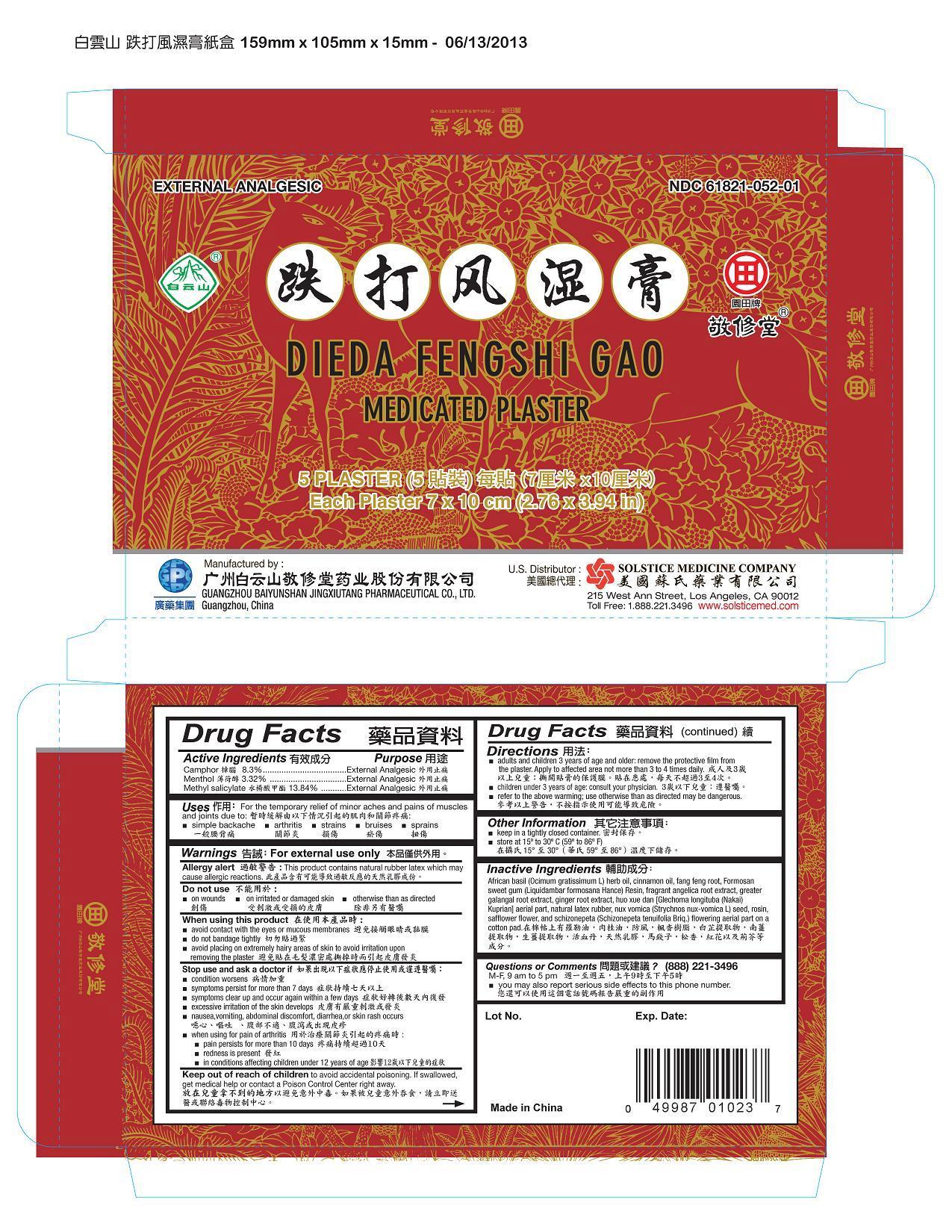 DRUG LABEL: DIEDA FENGSHI GAO MEDICATED
NDC: 61821-052 | Form: PLASTER
Manufacturer: GUANGZHOU BAIYUNSHAN JINGXIUTANG PHARMACEUTICAL COMPANY
Category: otc | Type: HUMAN OTC DRUG LABEL
Date: 20191114

ACTIVE INGREDIENTS: CAMPHOR (SYNTHETIC) 8.3 g/1 1; MENTHOL 3.32 g/1 1; METHYL SALICYLATE 13.84 g/1 1
INACTIVE INGREDIENTS: OCIMUM GRATISSIMUM WHOLE; CINNAMON OIL; SAPOSHNIKOVIA DIVARICATA ROOT; LIQUIDAMBAR FORMOSANA RESIN; GREATER GALANGAL; GINGER; GLECHOMA LONGITUBA TOP; NATURAL LATEX RUBBER; STRYCHNOS NUX-VOMICA SEED; ROSIN; SAFFLOWER; NEPETA TENUIFOLIA FLOWERING TOP

Drug Facts

Active ingredients
Camphor 8.3%
Menthol 3.32%
Methyl salicylate 13.84%

Purpose
External analgesic

Uses
For the temporary relief of minor aches and pains of muscles and joints
due to: ■ simple backache ■ arthritis ■ strains ■ bruises ■ sprains

Warnings

For external use only
Allergy alert: This product contains natural rubber latex which may cause allergic reactions

Do not use
■ on irritated or damaged skin ■ on wounds ■ otherwise than as directed

When using this product
■ avoid contact with the eyes or mucous membranes
■ do not bandage tightly
■ avoid placing on extremely hairy areas of skin to avoid irritation upon removing the plaster

Stop use and ask a doctor if
■ condition worsens
■ symptoms persist for more than 7 days
■ symptoms clear up and occur again within a few days
■ excessive irritation of the skin develops
■ nausea, vomiting, abdominal discomfort, diarrhea, or skin rash occurs
■ when using for pain of arthritis:
■ pain persists for more than 10 days ■ redness is present
■ in conditions affecting children under 12 years of age

Keep out of reach of children to avoid accidental poisoning.
If swallowed, get medical help or contact a Poison Control Center right away.

Directions
■ adults and children 3 years of age and older: remove the attached film from the plaster. Apply to affected area not more than 3 to 4 times daily
■ children under 3 years of age: consult your physician
■ refer to the above warnings; use otherwise than as directed may be dangerous

Other information
■ keep in a tightly closed container
■ store at 15º to 30º C (59º to 86º F)

Inactive ingredients
African basil (Ocimum gratissimum L) herb oil, cinnamon oil, fang feng root, Formosan sweet gum (Liquidambar formosana Hance) Resin,
fragrant angelica root extract, greater galangal root extract, ginger root extract, huo xue dan [Glechoma longituba (Nakai) Kuprian] aerial part,
natural latex rubber, nux vomica (Strychnos nux-vomica L) seed, rosin, safflower flower, and schizonepeta (Schizonepeta tenuifolia Briq.) flowering
aerial part on a cotton pad.

Questions or comments? (888) 221-3496 M-F 9 am to 5 pm
■ you may also report serious side effects to this phone number

PACKAGE LABEL

EXTERNAL ANALGESIC

NDC 61821-052-01
DIEDA FENGSHI GAO MEDICATED PLASTER
5 Plasters per Carton
Each Plaster 7x10 cm (2.76 x 3.94 in)